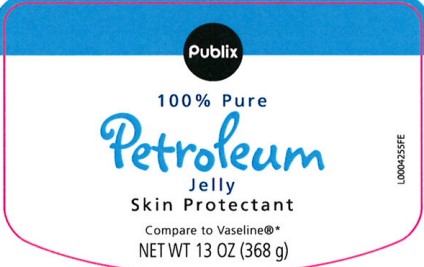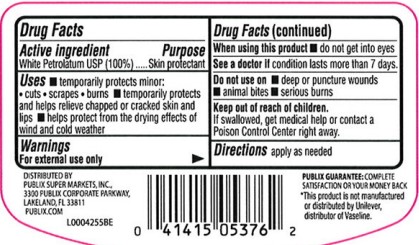 DRUG LABEL: Petroleum Skin Protectant
NDC: 56062-069 | Form: JELLY
Manufacturer: Publix Super Markets, Inc.
Category: otc | Type: HUMAN OTC DRUG LABEL
Date: 20260205

ACTIVE INGREDIENTS: PETROLATUM 1 g/1 g

Publix 069.001/069AA
Petroleum Jelly

active ingredient

White Petrolatum USP (100%)

Purpose

Skin protectant

Uses

- temporarily protects minor: cuts, scrapes, burns
- temporarily protects and helps relieve chapped or cracked skin and lips
- helps protect from the drying effects of wind and cold weather

Warnings

For external use only

When using this product

- do not get into eyes

See a doctor if

condition lasts more than 7 days.

Do not use

- deep or puncture wounds
- animal bites
- serious burns

Keep out of reach of children.

If swallowed, get medical help or contact a Poison Control Center right away.

Directions

apply as needed

Inactive Ingredients

None

Dislcaimer

*This product is not manufactured or distributed by Unliever, distributor of Vaseline.

Adverse Reactions

Distributed by

Publix Super Markets, Inc

3300 Publix Corporate Parkway

Lakeland, FL 33811

publix.com

PUBLIX GUARANTEE: COMPLETE SATISFACTION OR YOUR MONEY BACK

Principal display panel

Publix

100% PURE

petroleum

JELLY

Skin Protectant

Compare to Vaseline® *

NET WT 13 OZ (368 g)